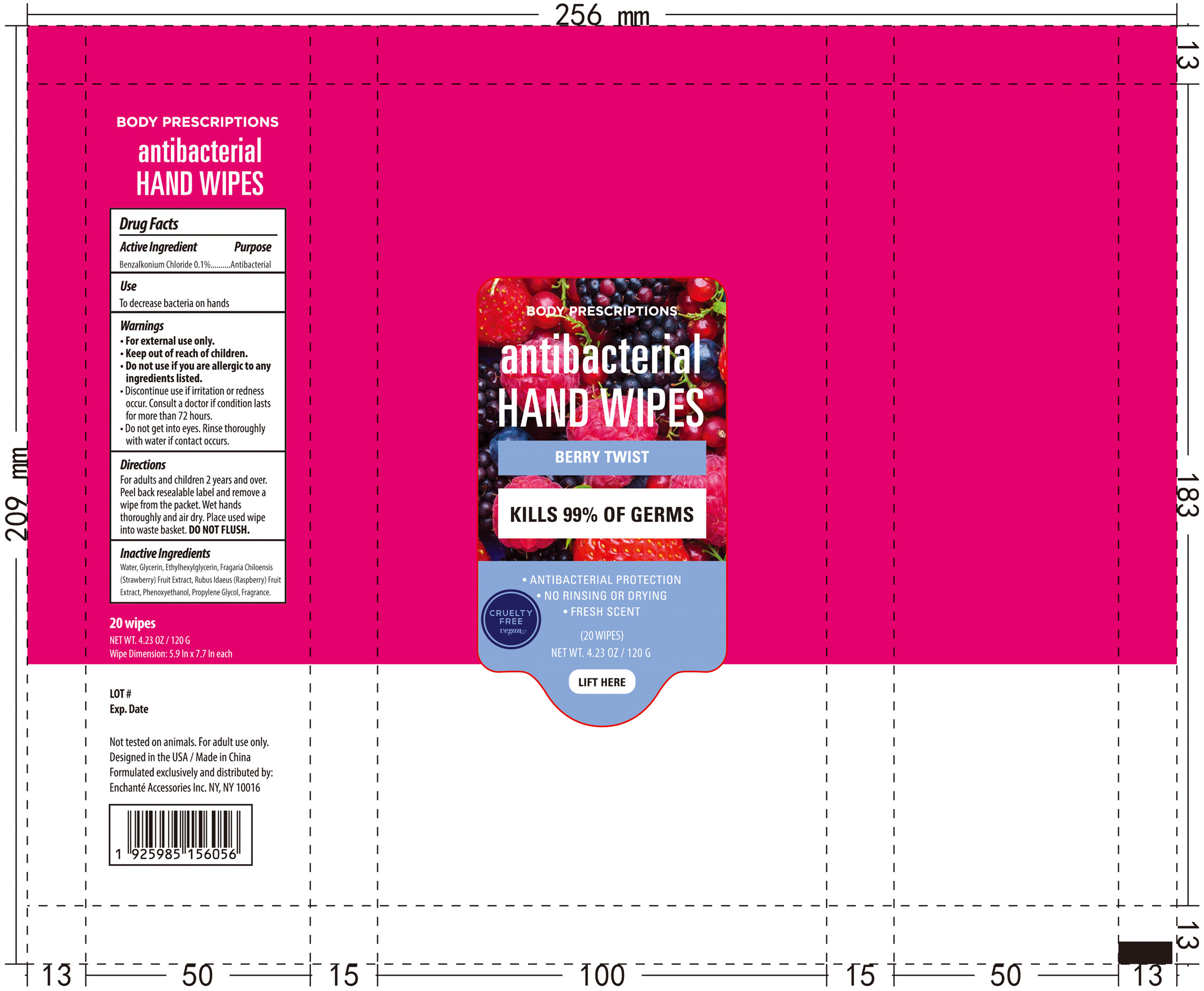 DRUG LABEL: BODY PRESCRIPTIONS Antibacterial Hand Wipes BERRY TWIST
NDC: 50563-245 | Form: SOLUTION
Manufacturer: ENCHANTE ACCESSORIES INC.
Category: otc | Type: HUMAN OTC DRUG LABEL
Date: 20200819

ACTIVE INGREDIENTS: BENZALKONIUM CHLORIDE 4.5 mg/1 1
INACTIVE INGREDIENTS: GLYCERIN; ETHYLHEXYLGLYCERIN; FRAGARIA CHILOENSIS WHOLE; PHENOXYETHANOL; PROPYLENE GLYCOL; RUBUS IDAEUS WHOLE; WATER

G0ABCW13

Active Ingredient

Benzalkonium Chloride 0.1%

Purpose

Antibacterial

Use

■ To decrease bacteria on hands

WARNINGS

For external use only

Stop Use

Do not use if you are allergic to any ingredients listed

Discontinue use if irritation or redness occur. Consult a doctor if condition lasts for more than 72 hours

Do not get into eyes. Rinse thoroughly with water if contact occurs

keep out of reach of children

Directions

For adults and children two years and over

Peel back reusable label and remove a wipe from the packet.

Wet hands thoroughly and air dry.

Place used wipes in to waste basket. Do not flush.

Inactive ingredients

Water, Glycerin, Ethylhexylglycerin, Fragaria Chiloensis (Strawberry) Fruit Extract, Rubus Idaeus (Raspberry) Fruit Extract, Phenoxyethanol, Propylene Glycol, Fragrance